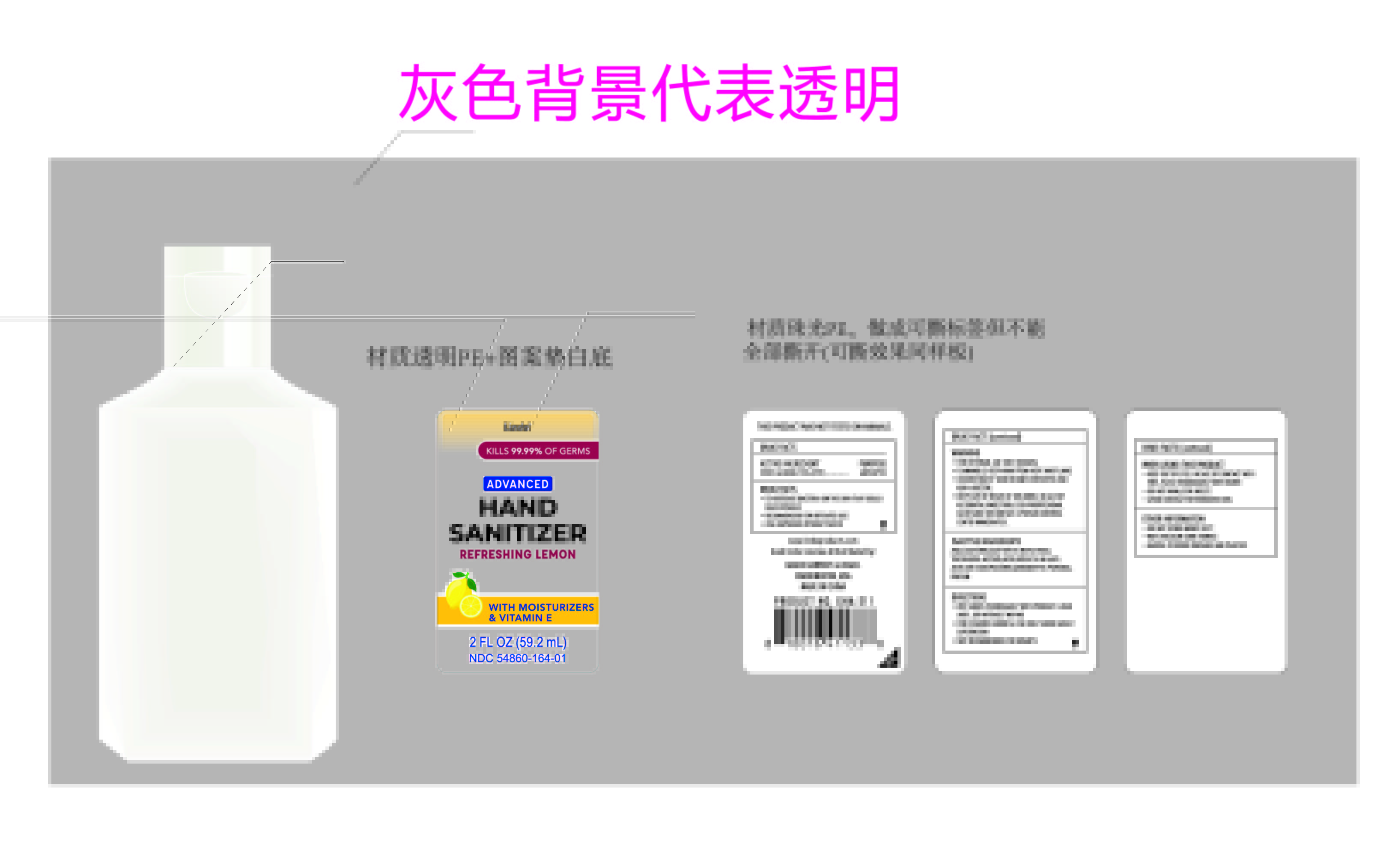 DRUG LABEL: Lindo hand sanitizer 59.2ml with refreshing lemon GHA-211
NDC: 54860-164 | Form: LIQUID
Manufacturer: Shenzhen Lantern Scicence Co Ltd
Category: otc | Type: HUMAN OTC DRUG LABEL
Date: 20200418

ACTIVE INGREDIENTS: ALCOHOL 75 mL/100 mL
INACTIVE INGREDIENTS: .ALPHA.-TOCOPHEROL ACETATE 0.01 mL/100 mL; LEMON 0.15 mL/100 mL; ALOE ANDONGENSIS WHOLE 0.1 mL/100 mL; AMINOMETHYLPROPANOL 0.09 mL/100 mL; WATER 23.85 mL/100 mL; GLYCERIN 0.5 mL/100 mL; CARBOMER INTERPOLYMER TYPE A (55000 CPS) 0.3 mL/100 mL

Lindo hand sanitizer 59.2ml with refreshing lemon GHA-211

Active Ingredient

Active Ingredient purpose

Ethyl Alcohol 75%(v/v) Antiseptic

drug facts

To decrease bacteria on the skin that could cause disease.

Recommended for repeated use

Use anywhere without water.

DOSAGE AND ADMINISTRATION

Recommended for repeated use.

use anywhere without water.

Warning

For external use only(hands)

Flammable,keep away from heat and flame.

discontinue if skin becomes irritated andask a doctor.

Keep out of reach of children.In case of accidental ingestion,seek proffesional assistance or contact a poison control center immediately.

WARNINGS AND PRECAUTIONS

For external use only.

Flammable, keep away from heat and flame.

STOP USE

Discontinue if skin becomes irritated and ask a doctor .

Keep out of reach of children. In case of accidental ingestion, seek professional assistance or contact a poson control center immediately.

Inactive ingredients

Water, Glycerin,Aloe Yohjyu Matsu Ekisu,Tocopheryl Acetate,Acrylates/C10-30 Alkyl Acrylate Crosspolymer,Aminomethyl Propanol,Parfum.

Directions

Wet hands thoroughly with product and rub until dry without wiping

For children under 6,use only under adult supervision.

Not recommended for infants.

When using this product

Keep out of eyes,in case of contact with eyes,flush thoroughly with water

Do not inhale or ingest

Avoid contact with broken skin

When using this product

keep out of eyes. In case of contact with eyes, flush thoroughly with water.

Do not inhale or ingest.

Avoid contact with broken skin.

Other information

Do not store above 105F.

May discolor some fabrics.

Harmful to wood finishes and plastics.

other information

Do not srore above 105℉

May discolor some fabrics

Harmful to wood finishes and plastics